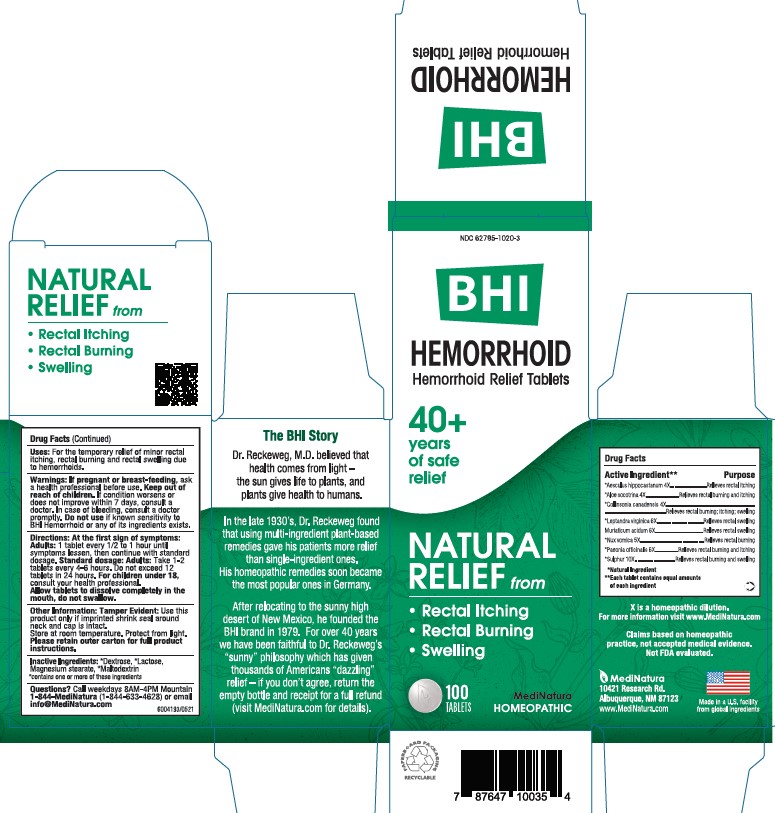 DRUG LABEL: BHI Hemorrhoid
NDC: 62795-1020 | Form: TABLET
Manufacturer: MediNatura Inc
Category: homeopathic | Type: HUMAN OTC DRUG LABEL
Date: 20220105

ACTIVE INGREDIENTS: HORSE CHESTNUT 4 [hp_X]/1 1; ALOE 4 [hp_X]/1 1; COLLINSONIA CANADENSIS ROOT 4 [hp_X]/1 1; VERONICASTRUM VIRGINICUM ROOT 6 [hp_X]/1 1; HYDROCHLORIC ACID 6 [hp_X]/1 1; STRYCHNOS NUX-VOMICA SEED 5 [hp_X]/1 1; PAEONIA OFFICINALIS ROOT 6 [hp_X]/1 1; SULFUR 10 [hp_X]/1 1
INACTIVE INGREDIENTS: LACTOSE; MAGNESIUM STEARATE; MALTODEXTRIN; DEXTROSE

BHI Hemorrhoid Tablet

ACTIVE INGREDIENTS

Each tablet contains: *Aesculus hippocastanum 4X, *Aloe socotrina 4X, *Collinsonia canadensis 4X, *Leptandra virginica 6X, Muriaticum acidum 6X, *Nux vomica 5X, *Paeonia officinalis 6X, *Sulphur 10X 37.5 mg each.

*Natural Ingredients

INACTIVE INGREDIENTS

Inactive Ingredients: **Dextrose, ** Lactose, Magnesium Stearate, **Maltodextrin
**contains one or more of these ingredients.

PURPOSE

Relieves Hemorrhoid Discomfort

• Rectal Itching

• Rectal Burning

• Swelling

USES

For the temporary relief of minor rectal itching, rectal burning, rectal swelling due to hemorrhoids

DIRECTIONS

At first sign of symptoms:
Adults: 1 tablet every 1/2 to 1 hour until symptoms lessen,
then continue with standard dosage.
Standard dosage: Adults: Take 1-2 tablets every 4 to 6 hours.
Do not exceed 12 tablets in 24 hours. For children under 18,
consult your health professional.
Allow tablets to dissolve completely in the mouth, do not swallow.

WARNINGS

If pregnant or breast-feeding, ask a health professional before use. Keep out of reach of children. If condition worsens or does not improve within 7 days, consult a doctor. In case of bleeding, consult a doctor promptly. Do not use if known sensitivity to Hemorrhoid or any of its ingredients exists.

KEEP OUT OF REACH OF CHILDREN